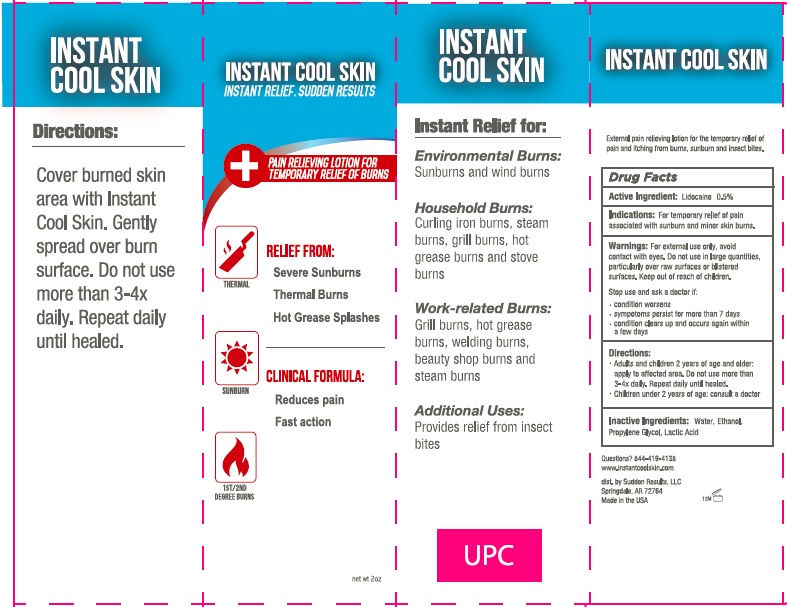 DRUG LABEL: Instant Cool Skin
NDC: 66428-007 | Form: LOTION
Manufacturer: Therapon Skin Health, LP
Category: otc | Type: HUMAN OTC DRUG LABEL
Date: 20150615

ACTIVE INGREDIENTS: LIDOCAINE .5 g/100 mL
INACTIVE INGREDIENTS: WATER; ALCOHOL; PROPYLENE GLYCOL; LACTIC ACID 

Active Ingredients

Lidocaine 0.5%

Uses

External Analgesic

Indications

For temporary relief of pain associated with sunburn and minor skin burns.

Warnings

For external use only, avoid contact with eyes. Do not use in large quantities, particularly over raw surfaces or blistered surfaces

Keep out of reach of children.

Stop use and ask a doctor if:

- condition worsens
- symptoms persist for more than 7 days
- condition clears up and occurs again within a few days

Directions

- Adults and children 2 years and older: apply to affected area. Do not use more than 3-4x daily. Repeat daily until healed.
- Children under 2 years of age: consult a doctor

Inactive Ingredients

Water, Ethanol, Propylene Glycol, Lactic Acid